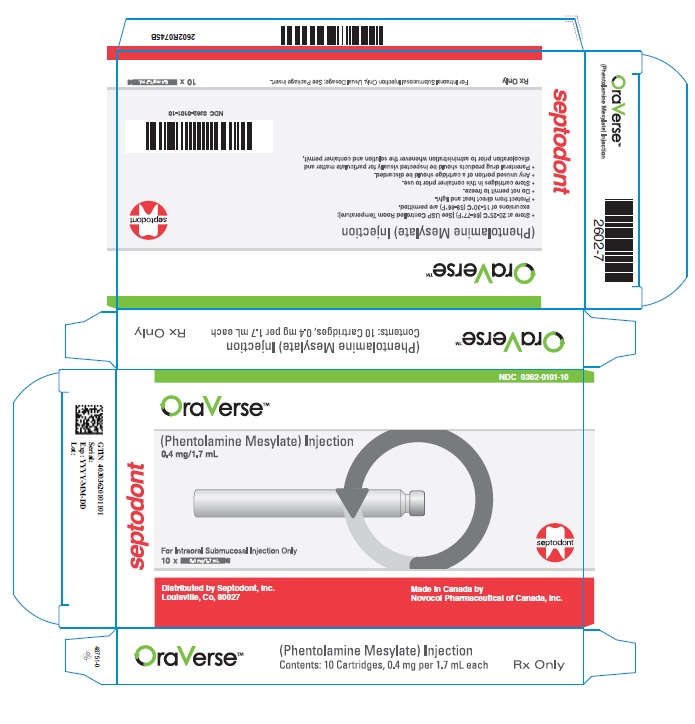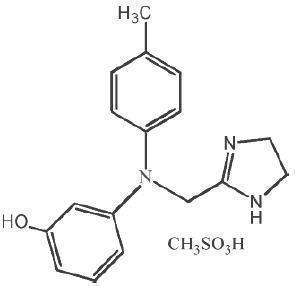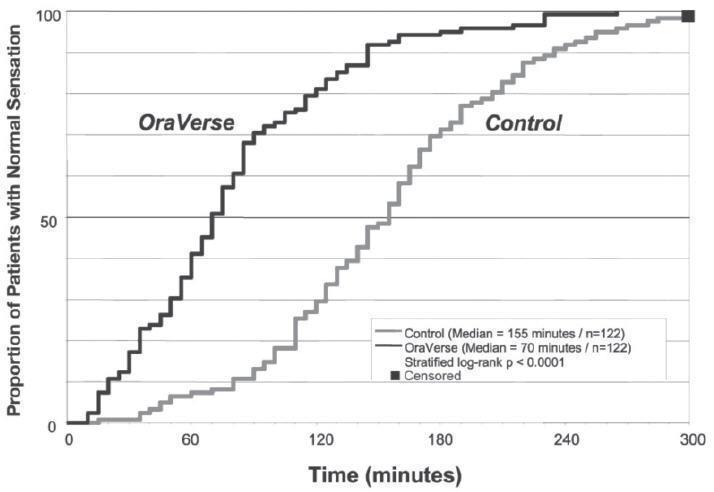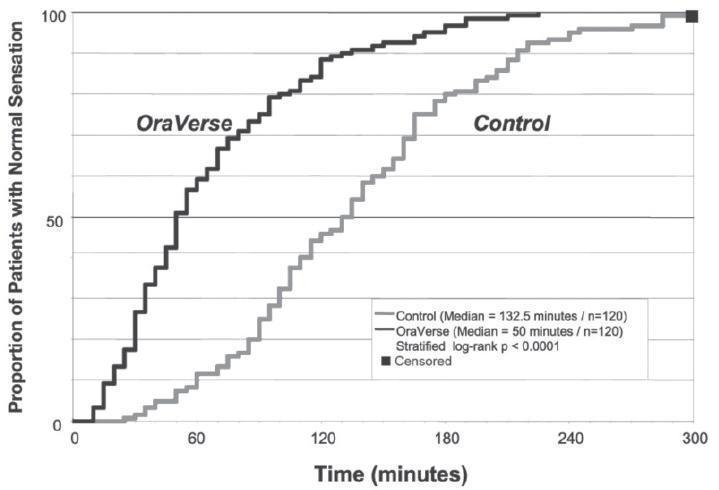 DRUG LABEL: Oraverse
NDC: 0362-0101 | Form: INJECTION, SOLUTION
Manufacturer: Septodont, Inc.
Category: prescription | Type: HUMAN PRESCRIPTION DRUG LABEL
Date: 20181205

ACTIVE INGREDIENTS: Phentolamine Mesylate 0.235 mg/1 mL
INACTIVE INGREDIENTS: Edetate Disodium 0.5 mg/1 mL; Mannitol 50 mg/1 mL; Sodium Acetate 1.36 mg/1 mL; Water; Acetic Acid; Sodium Hydroxide; Nitrogen

HIGHLIGHTS OF PRESCRIBING INFORMATION

These highlights do not include all the information needed to use OraVerse™ safely and effectively. See full prescribing information for OraVerse.
OraVerse (phentolamine mesylate) Injection
Initial U.S. Approval: 1952

1. INDICATONS AND USAGE

OraVerse, an alpha adrenergic blocker, is indicated for adult and pediatric patients ages 3 years and older for the reversal of soft-tissue anesthesia, i.e., anesthesia of the lip and tongue, and the associated functional deficits resulting from an intraoral submucosal injection of a local anesthetic containing a vasoconstrictor. (1)

2. DOSAGE AND ADMINISTRATION

Amount of Local Anesthetic Administered | Dose of OraVerse
^1/4 Cartridge | ^1/4 Cartridge (0.1 mg)
½ Cartridge | ½ Cartridge (0.2 mg)
1 Cartridge | 1 Cartridge (0.4 mg)
2 Cartridges | 2 Cartridges (0.8 mg)

OraVerse is administered using the same location(s) and same technique(s) (infiltration or block injection) used for the administration of local anesthetic. (2.1)

3. DOSAGE FORMS AND STRENGTHS

0.4 mg/1.7 mL solution per cartridge (3)

4. CONTRAINDICATIONS

OraVerse is contraindicated in patients with:
Hypersensitivity to the active substance or to any ingredients in the formulation. (4)

5. WARNINGS AND PRECAUTIONS

Myocardial infarction, cerebrovascular spasm, and cerebrovascular occlusion have been reported to occur following the intravenous or intramuscular administration of phentolamine, usually in association with marked hypotensive episodes or shock-like states which occasionally follow parenteral administration.

Tachycardia and cardiac arrhythmiasmay occur with the use of phentolamine or other alpha-adrenergic blocking agents. (5.1)

6. ADVERSE REACTIONS

The most common adverse reaction with OraVerse (incidence ≥5% and > control) is injection-site pain. (6)

To report SUSPECTED ADVERSE REACTIONS, contact Septodont at 1-888-888-1441 or FDA at 1-800-FDA-1088 or www.fda.gov/medwatch.

8. USE IN SPECIFIC POPULATIONS

- Use in pediatric patients less than 3 years of age or <15 kg (33 lbs) has not been established. (8.4)
- In pediatric patients weighing at least 10 kg (22 lbs), the maximum dose of OraVerse recommended is 1/4cartridge (0.1 mg). (8.4)

FULL PRESCRIBING INFORMATION

1. INDICATONS AND USAGE

OraVerse an alpha adrenergic blocker, is indicated for adult and pediatric patients ages 3 years and older for the reversal of soft-tissue anesthesia, i.e., anesthesia of the lip and tongue, and the associated functional deficits resulting from an intraoral submucosal injection of a local anesthetic containing a vasoconstrictor.

2. DOSAGE AND ADMINISTRATION

2.1 General Dosing information

The recommended dose of OraVerse is based on the number of cartridges of local anesthetic with vasoconstrictor administered:

Amount of Local Anesthetic Administered | Dose of OraVerse [mg] | Dose of OraVerse [Cartridge(s)]
^1/4 Cartridge | 0.1 | ^1/4
½ Cartridge | 0.2 | ½
1 Cartridge | 0.4 | 1
2 Cartridges | 0.8 | 2

OraVerse should be administered following the dental procedure using the same location(s) and technique(s) (infiltration or block injection) employed for the administration of the local anesthetic.

Chemically disinfect the carpule cap by wiping with either isopropyl alcohol (91%) or ethyl alcohol (70%). Many commercially available brands of isopropyl (rubbing) alcohol, as well as solutions of ethyl alcohol not of U.S.P. grade, contain denaturants that are injurious to rubber and therefore are not to be used. Inspect carpules visually prior to administration and do not use if particulate matter, discoloration, cracks in the glass, protruding plungers or other defects are observed.

Note: Do not administer OraVerse if particulate matter, discoloration, cracks in the glass, protruding plungers or other defects are observed.

2.2 Dosing in Special Populations

In pediatric patients weighing between ≥15 kg and <30 kg, the maximum dose of OraVerse recommend is ½ cartridge (0.2 mg).
(Note: Use in pediatric patients under 3years of age or weighing less than15 kg (33 lbs) is not recommended. A dose of more than 1 cartridge [0.4 mg] of OraVerse has not been studied in children less than 4 years of age.)

3. DOSAGE FORMS AND STRENGTHS

0.4 mg/1.7 mL solution per cartridge

4. CONTRAINDICATIONS

OraVerse is contraindicated in patients with:
Hypersensitivity to the active substance or to any ingredients in the formulation

5. WARNINGS AND PRECAUTIONS

5.1 Cardiovascular Events

Myocardial infarction, cerebrovascular spasm, and cerebrovascular occlusion have been reported to occur following the parenteral administration of phentolamine. These events usually occurred in association with marked hypotensive episodes producing shock-like states.

Tachycardia and cardiac arrhythmias may occur with the use of phentolamine or other alpha-adrenergic blocking agents. Although such effects are uncommon after administration of OraVerse, clinicians should be alert to the signs and symptoms of these events, particularly in patients with a prior history of cardiovascular disease.

6. ADVERSE REACTIONS

In clinical trials, the most common adverse reaction with OraVerse that was greater than the control group was injection site pain.

6.1 Clinical Trials Experience

Because clinical trials are conducted under widely varying conditions, adverse reaction rates observed in the clinical trials of a drug cannot be directly compared to rates in the clinical trials of another drug and may not reflect the rates observed in practice.

Dental patients were administered a dose of either 0.2, 0.4 or 0.8mg of OraVerse. The majority of adverse reactions were mild and resolved within 48 hours. There were no serious adverse reactions and no discontinuations due to adverse reactions.

Table 1 lists adverse reactions where the frequency was greater than or equal to 3% in any OraVerse dose group and was equal to or exceeded that of the control group.

Table 1: Adverse Reactions with Frequency Greater Than or Equal to 3% and Equal to or Exceeding Control
Adverse Event | OraVerse |  | Control
 | 0.2 mg (N = 83) | 0.4 mg (N = 284) | 0.8 mg (N = 51) | Total (N = 418) | Total (N = 359)
 | N (%) | N (%) | N (%) | N (%) | N (%)
Patients with AEs | 15 (18) | 82 (29) | 20 (39) | 117 (28) | 96 (27)
Tachycardia | 0 (0) | 17 (6) | 2 (4) | 19 (5) | 20 (6)
Bradycardia | 0 (0) | 5 (2) | 2 (4) | 7 (2) | 1 (0.3)
Injection site pain | 5 (6) | 15 (5) | 2 (4) | 22 (5) | 14 (4)
Post procedural pain | 3 (4) | 17 (6) | 5 (10) | 25 (6) | 23 (6)
Headache | 0 (0) | 10 (4) | 3 (6) | 13 (3) | 14 (4)

An examination of population subgroups did not reveal a differential adverse reaction incidence on the basis of age, gender, or race.

Results from the pain assessments in Study 1 and Study 2, involving mandibular and maxillary procedures, respectively, indicated that the majority of dental patients in both OraVerse and control groups experienced no or mild oral pain, with less than 10% of patients in each group reporting moderate oral pain with a similar distribution between the OraVerse and control groups. No patient experienced severe pain in these studies.

Study 4 included 150 pediatric patients between 2-5 years of age who received a dose of either ¼ cartridge (0.1 mg), ½ cartridge (0.2 mg) or 1 cartridge (0.4 mg) of OraVerse or sham injection (placebo). Safety in patients in Study 4 was similar to safety in older patients described above. Post-procedural revealed that oral pain was reported in the OraVerse group with a higher frequency (10.1%) than the placebo group (3.9%). The proportion of patients in the OraVerse and placebo groups was comparable with respect to the highest severity of pain experienced: 30.4% of OraVerse patients and 30% of placebo patients reported no pain; 43.1% of OraVerse patients and 45.0% of placebo patients reported mild pain; 19.0% of OraVerse subjects and 17.5% of placebo patients reported moderate pain; and 15.2% of OraVerse patients and 15.0% of placebo patients reported severe pain.

6.2 Adverse Reactions in Clinical Trials

Adverse reactions reported by less than 3% but at least 2 dental patients receiving OraVerse and occurring at a greater incidence than those receiving control, included diarrhea, facial swelling, increased blood pressure/hypertension, injection site reactions, jaw pain, oral pain, paresthesia, pruritus, tenderness, upper abdominal pain and vomiting. The majority of these adverse reactions were mild and resolved within 48 hours. The few reports of paresthesia were mild and transient and resolved during the same time period.

6.3 Post Marketing Adverse Reactions Reports from Literature and Other Sources

The following adverse reactions have been identified during postapproval parenteral use of phentolamine mesylate. Because these reactions are reported voluntarily from a population of uncertain size, it is not always possible to reliably estimate their frequency or establish a causal relationship to drug exposure.

Acute and prolonged hypotensive episodes and cardiac arrhythmias have been reported with the use of phentolamine. In addition, weakness, dizziness, flushing, orthostatic hypotension, and nasal stuffiness have occurred.

7. DRUG INTERACTIONS

There are no known drug interactions with OraVerse.

7.1 Lidocaine and Epinephrine

When OraVerse was administered as an intraoral submucosal injection 30 minutes after injection of a local anesthetic, 2% lidocaine HCl with 1:100,000 epinephrine, the lidocaine concentration increased immediately after OraVerse intraoral injection. Lidocaine AUC and Cmax values were not affected by administration of OraVerse. OraVerse administration did not affect the PK of epinephrine.

8. USE IN SPECIFIC POPULATIONS

8.1 Pregnancy

Pregnancy Category C

Risk summary

There are no available data with OraVerse in pregnant women to inform a drug-associated risk for major birth defects and miscarriage. In animal toxicology studies, phentolamine administered orally to pregnant mice and rats during the period of organogenesis resulted in skeletal immaturity and decreased growth in the offspring at doses at least 24-times the recommended dose. Additionally, a lower rate of implantation was seen in pregnant rats treated with phentolamine at least 60-times the recommended dose. No malformations or embryofetal deaths were observed in the offspring of pregnant mice, rats, and rabbits administered phentolamine during the period of organogenesis at doses 24-, 60-, and 20-times, respectively, the recommended dose [see Data].
The estimated background risk of major birth defects and miscarriage for the indicated population is unknown. In the U.S. general population, the estimated background risk of major birth defects and miscarriage in clinically recognized pregnancies is 2-4% and 15-20%, respectively.

Data

Animal Data

Oral administration of phentolamine to pregnant rats and mice at doses at least 24-times the recommended dose (based on a mg/m2 comparison with a 60 kg human) resulted in slightly decreased growth and slight skeletal immaturity of the fetuses. Immaturity was manifested by increased incidence of incomplete or unossified calcanei and phalangeal nuclei of the hind limb and of incompletely ossified sternebrae. At oral phentolamine doses at least 60-times the recommended dose (based on a mg/m2 comparison with a 60 kg human),a slightly lower rate of implantation was found in the rat. Phentolamine did not affect embryonic or fetal development in the rabbit at oral doses at least 20-times the recommended dose (based on a mg/m2 comparison with a 60 kg human). No malformations or embryofetal deaths were observed in the rat, mouse or rabbit studies.

8.2 Lactation

Risk Summary
There is no information regarding the presence of phentolamine in human milk, the effects on the breastfed infant or the effects on milk production. The developmental and health benefits of breastfeeding should be considered along with the mother’s clinical need for OraVerse and any potential adverse effects on the breastfed infant from OraVerse, or from the underlying maternal condition.

8.4 Pediatric Use

The safety and efficacy of OraVerse has not been established in patients younger than 3 years.
The safety and effectiveness of OraVerse in pediatric patients ages 3 years and older is supported by evidence from adequate and well-controlled studies of OraVerse in adults, with additional adequate and well-controlled studies of OraVerse in pediatric patients ages 12-17 years old [Studies 1 (mandibular procedures) and 2 (maxillary procedures)], ages 6-11 years old [Study 3 (mandibular and maxillary procedures)], and another study in patients ages 2-5 years [Study 4]. Study 4 assessed safety and effectiveness in patients 4 to 5 years, but was not designed to demonstrate efficacy. Use in patients 3 to <4 years is supported by similar pharmacokinetics and safety in these patients compared with older pediatric patients (see Clinical Pharmacology (12.3)]. Use of OraVerse in this age group (3 to < 4 years) is also supported by the similarity in the exposure response of OraVerse for pediatric and adult patients, and the adequacy of the safety database for patients age ≥ 3. The safety database for patients age < 3 is limited, and therefore, use in patients age < 3 is not recommended. Dosages in pediatric patients may need to be limited based on body weight. [see Dosage and Administration (2)]

8.5 Geriatric Use

Of the total number of patients in clinical studies of OraVerse, 55 were 65 and over, while 21 were 75 and over. No overall differences in safety or effectiveness were observed between these patients and younger patients, and other reported clinical experience has not identified differences in responses between the elderly and younger patients, but greater sensitivity of some older individuals cannot be ruled out.

10. OVERDOSAGE

No deaths due to acute poisoning with phentolamine have been reported.

Overdosage with parenterally administered phentolamine is characterized chiefly by cardiovascular disturbances, such as arrhythmias, tachycardia, hypotension, and possibly shock. In addition, the following might occur: excitation, headache, sweating, pupillary contraction, visual disturbances, nausea, vomiting, diarrhea, or hypoglycemia.

There is no specific antidote; treatment consists of appropriate monitoring and supportive care. Substantial decreases in blood pressure or other evidence of shock-like conditions should be treated vigorously and promptly.

11. DESCRIPTION

Phentolamine mesylate is phenol,3-[[(4,5-dihydro-1H-imidazol-2-yl)methyl](4-methyl-phenyl)amino]-,methanesulfonate (salt), a non-specific alpha adrenergic blocker.

Phentolamine mesylate USP is a white to off-white, odorless crystalline powder with a molecular weight of 377.46. It is sparingly soluble in water, soluble in alcohol, and slightly soluble in chloroform. The empirical formulation is C17H19N3O•CH4O3S, and the chemical structure is:

OraVerse (phentolamine mesylate) Injection is a clear, colorless, sterile, non pyrogenic, isotonic, preservative free solution. Each 1.7 mL cartridge contains 0.4 mg phentolamine mesylate, D-mannitol, edetate disodium, and sodium acetate. Either acetic acid or sodium hydroxide is used as necessary to adjust the pH.

12. CLINICAL PHARMACOLOGY

12.1 Mechanism of Action

The mechanism by which OraVerse accelerates reversal of soft-tissue anesthesia and the associated functional deficits is not fully understood. Phentolamine mesylate, the active ingredient in OraVerse, produces an alpha-adrenergic block of relatively short duration resulting in vasodilatation when applied to vascular smooth muscle. In an animal model, OraVerse increased local blood flow in submucosal tissue of the dog when given after an intraoral injection of lidocaine 2% with 1:100,000 epinephrine.

12.3 Pharmacokinetics

Following OraVerse administration, phentolamine is 100% available from the submucosal injection site and peak concentrations are achieved 10-20 minutes after injection. Phentolamine systemic exposure increased linearly after 0.8 mg compared to 0.4 mg OraVerse intraoral submucosal injection. The terminal elimination half-life of phentolamine in the blood was approximately 2-3 hours.

Pediatrics

Following OraVerse administration, the phentolamine Cmax was higher (approximately 3.5-fold) in children who weighed between 15 and 30 kg (33 and 66 lbs) than in children who weighed more than 30 kg. However, phentolamine AUC was similar between the two groups. It is recommended that in children weighing 15-30 kg, the maximum dose of OraVerse should be limited to ½ cartridge (0.2 mg) (see Dosage and Administration section).

The pharmacokinetics of OraVerse in adults and in children who weighed more than 30 kg (66 lbs) are similar after intraoral submucosal injection.

OraVerse has not been studied in children under 3 years of age or weighing less than 15 kg (33 lbs). The pharmacokinetics of OraVerse after administration of more than 1 cartridge (0.4mg) has not been studied in children.

13. NONCLINICAL TOXICOLOGY

13.1 Carcinogenesis, Mutagenesis, Impairment of Fertility

Carcinogenesis
Carcinogenic studies with OraVerse have not been conducted.

Mutagenesis
Phentolamine was not mutagenic in the in-vitro bacterial reverse mutation (Ames) assay. In the in-vitro chromosomal aberration study in Chinese hamster ovary cells, numerical aberrations were slightly increased after a 4-hour exposure to phentolamine without metabolic activation and structural aberrations were slightly increased after a 4-hour exposure to phentolamine with metabolic activation only at the highest concentrations tested, but neither numerical nor structural aberrations were increased after a 20-hour exposure without metabolic activation. Phentolamine was not clastogenic in two in-vivo mouse micronucleus assays.

Impairment of Fertility
The effect of phentolamine on female fertility has not been studied. Male rats treated with oral phentolamine for nine weeks (four weeks prior to mating, 3 weeks during the mating period and 2 weeks after mating) were mated with untreated females. At doses up to 143-times human therapeutic exposure levels at the Cmax, no adverse effects on male fertility parameters or on reproductive parameters in the untreated females mated with the treated males were observed.

14. CLINICAL STUDIES

The safety and efficacy of OraVerse when used for reversal of soft-tissue anesthesia (STA), i.e., anesthesia of the lips and tongue following a dental procedure that required local anesthesia containing a vasoconstrictor, were evaluated in the following clinical studies. OraVerse-induced reversal of local anesthetic effects on the teeth, mandible and maxilla has not been assessed.

Two Phase 3, double-blinded, randomized, multi-center, controlled studies were conducted in dental patients who had mandibular (Study 1) or maxillary (Study 2) restorative or periodontal maintenance procedures and who had received a local anesthetic that contained a vasoconstrictor. The primary endpoint was time to normal lip sensation as measured by patient reported responses to lip palpation. The secondary endpoints included patients' perception of altered function, sensation and appearance, and their actual functional deficits in smiling, speaking, drinking and drooling, as assessed by both the patient and an observer blinded to the treatment. In the mandibular study, the time to recovery of tongue sensation was also a secondary endpoint. Patients were stratified by type and amount of anesthetic administered. OraVerse was administered at a cartridge ratio of 1:1 to local anesthetic. The control was a sham injection.

OraVerse reduced the median time to recovery of normal sensation in the lower lip by 85 minutes (55%) compared to control. The median time to recovery of normal sensation in the upper lip was reduced by 83 minutes (62%). The differences between these times for both studies are depicted in Kaplan-Meier plots for time to normal lip sensation in

Figures 1 and 2. Within 1 hour after administration of OraVerse, 41% of patients reported normal lower lip sensation as compared to 7% in the control group, and 59% of patients in the OraVerse group reported normal upper lip sensation as compared to 12% in the control group.

Figure 1: Kaplan-Meier Plot of Time to Recovery of Normal Sensation in the Lower Lip (ITT Analysis Data Set)

Figure 2: Kaplan-Meier Plot of Time to Recovery of Normal Sensation in the Upper Lip (ITT Analysis Data Set)

In Study 1 (mandibular), OraVerse accelerated: a) the recovery of the perception of normal appearance and function by 60 minutes (40%), b) the recovery of normal function by 60 minutes (50%), and c) the recovery of normal sensation in the tongue by 65 minutes (52%). In Study 2 (maxillary), the recovery of the perception of normal appearance and function was reduced by 60 minutes (50%) and the recovery of normal function was reduced by 45 minutes (43%).

Study 3, a pediatric, Phase 2, double-blinded, randomized, multi-center, controlled study was conducted in dental patients who had received 2% lidocaine with 1:100,000 epinephrine. Dental patients (n=152, ages 4-11 years) received 1/2 cartridge of OraVerse if they weighed ≥15 kg but <30 kg, and one-half or one full cartridge if they weighed ≥30 kg at a cartridge ratio of 1:1 to local anesthetic.
The median time to normal lip sensation in patients 6 to 11years of age who were trainable in the lip-palpation procedures, for mandibular and maxillary procedures combined, was reduced by 75 minutes (56%). Within 1 hour after administration of OraVerse, 44 patients (61%) reported normal lip sensation, while 9 patients (21%) randomized to the control group reported normal lip sensation. In this study, neither the patients' perception of their appearance or ability to function nor their actual ability to function was evaluated.

Study 4, a pediatric, Phase 4, double-blinded, randomized, multi-center, controlled study was conducted in dental patients undergoing mandibular and maxillary procedures after receiving 2% lidocaine with 1:100,000 epinephrine. Patients 2-5 years of age received sham injection (n=51) or 1/4 cartridge of OraVerse if they weighed ≥10 kg but <15kg (n=5), 1/2 cartridge if they weighed ≥15 kg but <30kg (n=91), and a full cartridge if they weighed >30kg (n=3). This study was not designed to demonstrate efficacy.

The median time to normal lip sensation in patients 4 and 5 years of age who were trainable in the lip-palpation procedure, for mandibular and maxillary procedures combined, was reduced by 48 minutes (44%). Within 2 hours after administration of OraVerse, 57 patients (80%) reported normal lip sensation, while 19 patients (51%) randomized to the sham injection group reported normal lip sensation. There were no significant differences between OraVerse and sham injection for time to return of normal function in pediatric functional assessment battery and time to recovery of normal tongue sensation (for mandibular procedures only).

16. HOW SUPPLIED/STORAGE AND HANDLING

OraVerse (phentolamine mesylate) Injection 0.4 mg/1.7 mL is supplied in a dental cartridge, in cartons of 10 and 50 cartridges. Each cartridge is individually packaged in a separate compartment of a 10 cartridge blister pack.

NDC 0362-0101-50
NDC 0362-0101-10

STORAGE AND HANDLING

Store at controlled room temperature, 20-25°C (68-77°F) with brief excursions permitted between 15-30°C (59-86°F) (see USP Controlled Room Temperature)

Protect from direct heat and light. Do not permit to freeze.

Manufactured by

Novocol Pharmaceutical of Canada, Inc.
Cambridge, Ontario, Canada

for

Septodont, Inc
Louisville, CO 80027

US Patent Nos.: 6,764,678; 6,872,390; 7,229,630
Trademark of Septodont Holdings SAS

17. PATIENT COUNSELING INFORMATION

Patients should be instructed not to eat or drink until normal sensation returns.

septodont

Rev. 03/16 (2604-5)

PRINCIPAL DISPLAY PANEL - 10 pack of 0.4mg/1.7 mL Carton

NDC 0362-0101-10

OraVerse™

(Phentolamine Mesylate) Injection
0.4 mg/1.7 mL

For Intraoral Submucosal Injection Only
10 x 0.4 mg/1.7 mL

septodont

Distributed by Septodont, Inc.
Louisville, CO, 80027

Made in Canada by
Novocol Pharmaceutical of Canada, Inc.